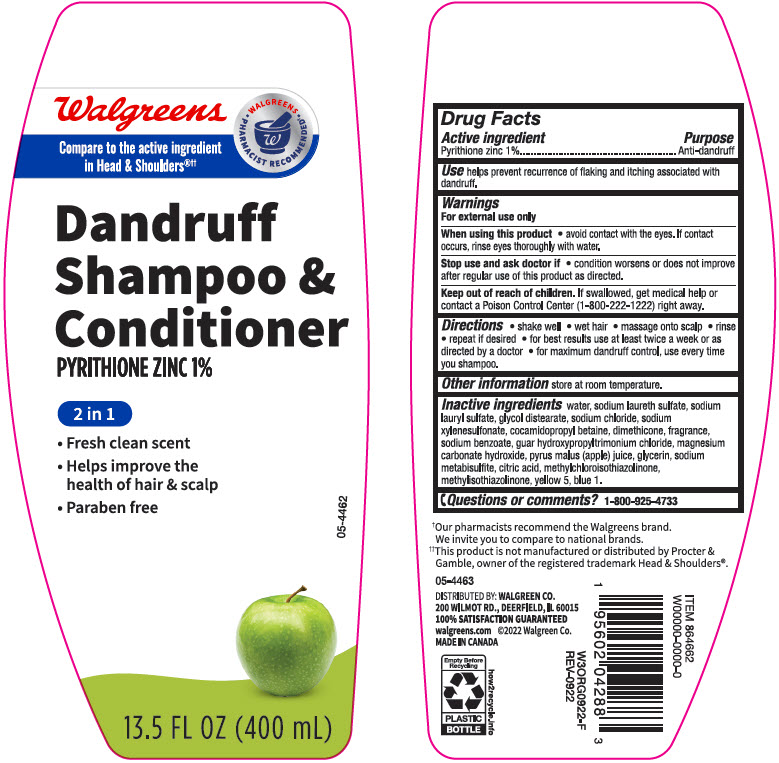 DRUG LABEL: Walgreens Dandruff Conditioner 2 in 1 Itchy Scalp
NDC: 0363-4288 | Form: SHAMPOO
Manufacturer: Walgreen Company
Category: otc | Type: HUMAN OTC DRUG LABEL
Date: 20241101

ACTIVE INGREDIENTS: Pyrithione Zinc 10 mg/1 mL
INACTIVE INGREDIENTS: Water; SODIUM LAURETH-3 SULFATE; Sodium Lauryl Sulfate; Glycol Distearate; Sodium Chloride; Sodium Xylenesulfonate; Cocamidopropyl Betaine; Dimethicone; Sodium Benzoate; GUAR HYDROXYPROPYLTRIMONIUM CHLORIDE; Magnesium Carbonate Hydroxide; APPLE JUICE; Glycerin; SODIUM METABISULFITE; CITRIC ACID MONOHYDRATE; Methylchloroisothiazolinone; Methylisothiazolinone; FD&C YELLOW NO. 5; FD&C BLUE NO. 1

Walgreens Dandruff Shampoo & Conditioner 2 in 1 Itchy Scalp
Anti-dandruff

Drug Facts

Active ingredient

Pyrithione Zinc 1%

Purpose

Anti-dandruff

Use

helps prevent recurrence of flaking and itching associated with dandruff.

Warnings

For external use only

When using this product

- avoid contact with the eyes. If contact occurs, rinse eyes thoroughly with water.

Stop use and ask a doctor if

- condition worsens or does not improve after regular use as directed.

Keep out of reach of children. If swallowed, get medical help or contact a Poison Control Center (1-800-222-1222) right away.

Directions

- shake well
- wet hair
- massage onto scalp
- rinse
- repeat if desired
- for best results use at least twice a week or as directed by a doctor
- for maximum dandruff control, use every time you shampoo.

Other information

store at room temperature

Inactive ingredients

water, sodium laureth sulfate, sodium lauryl sulfate, glycol distearate, sodium chloride, sodium xylenesulfonate, cocamidopropyl betaine, dimethicone, fragrance, sodium benzoate, guar hydroxypropyltrimonium chloride, magnesium carbonate hydroxide, pyrus malus (apple) juice, glycerin, sodium metabisulfite, citric acid, methylchloroisothiazolinone, methylisothiazolinone, yellow 5, blue 1.

Questions or Comments?

1-800-925-4733

DISTRIBUTED BY: WALGREEN CO.
200 WILMOT RD., DEERFIELD, IL 60015

PRINCIPAL DISPLAY PANEL - 400 mL Bottle Label

Walgreens

Compare to the active ingredient
in Head & Shoulders®††

• WALGREENS •
PHARMACIST RECOMMENDED†

Dandruff
Shampoo &
Conditioner
PYRITHIONE ZINC 1%

2 in 1

- Fresh clean scent
- Helps improve the
  health of hair & scalp
- Paraben free

05-4462

13.5 FL OZ (400 mL)